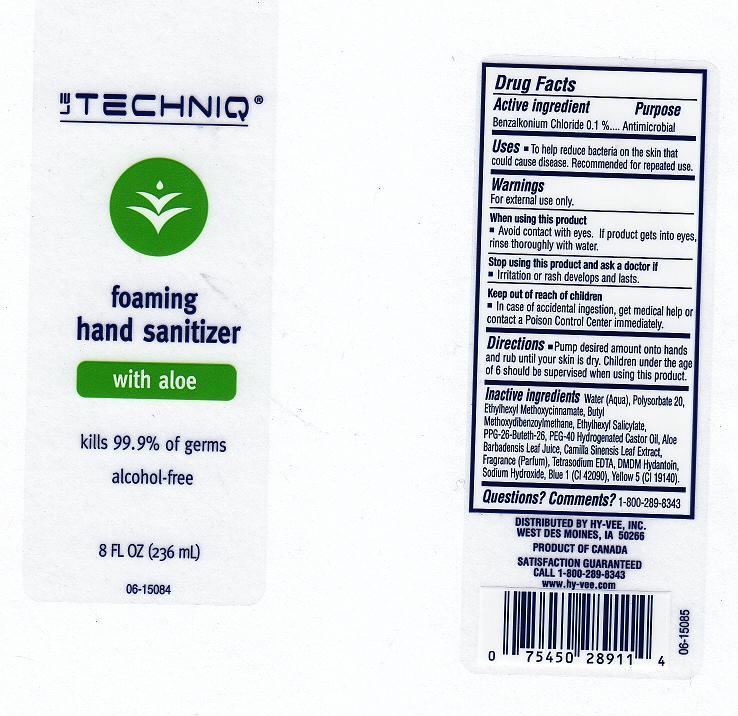 DRUG LABEL: FOAMING HAND SANITIZER
NDC: 42507-240 | Form: GEL
Manufacturer: HY-VEE INC
Category: otc | Type: HUMAN OTC DRUG LABEL
Date: 20111024

ACTIVE INGREDIENTS: BENZALKONIUM CHLORIDE 0.1 mL/100 mL
INACTIVE INGREDIENTS: WATER; POLYSORBATE 20; OCTINOXATE; AVOBENZONE; OCTISALATE; POLYOXYL 40 HYDROGENATED CASTOR OIL; ALOE VERA LEAF; GREEN TEA LEAF; EDETATE SODIUM; DMDM HYDANTOIN; SODIUM HYDROXIDE; FD&C BLUE NO. 1; FD&C YELLOW NO. 5

DRUG FACTS

ACTIVE INGREDIENT

BENZALKONIUM CHLORIDE 0.1 PERCENT

PURPOSE

ANTIMICROBIAL

USES

TO HELP REDUCE BACTERIA ON THE SKIN THAT COULD CAUSE DISEASE. RECOMMENDED FOR REPEATED USE.

WARNINGS

FOR EXTERNAL USE ONLY.

WHEN USING THIS PRODUCT

AVOID CONTACT WITH EYES. IF PRODUCT GETS INTO EYES, RINSE THOROUGHLY WITH WATER.

STOP USING THIS PRODUCT AND ASK DOCTOR IF

IRRITATION OR RASH DEVELOPS AND LASTS.

KEEP OUT OF REACH OF CHILDREN

IN CASE OF ACCIDENTAL INGESTION, GET MEDICAL HELP OR CONTACT A POISON CONTROL CENTER IMMEDIATELY.

DIRECTIONS

PUMP DESIRED AMOUNT ONTO HANDS AND RUB UNTIL YOUR SKIN IS DRY. CHILDREN UNDER THE AGE OF 6 SHOULD BE SUPERVISED WHEN USING THIS PRODUCT.

INACTIVE INGREDIENTS

WATER, POLYSORBATE 20, ETHYLHEXYL METHOXYCINNAMATE, BUTYL METHOXYDIBENZOYLMETHANE, ETHYLHEXYL SALICYLATE, PPG-26-BUTETH-26, PEG-40 HYDROGENATED CASTOR OIL, ALOE BARBADENSIS LEAF JUICE, FRAGRANCE, TETRASODIUM EDTA, DMDM HYDANTOIN, SODIUM HYDROXIDE, BLUE 1 (CI 42090), YELLOW 5 (CI 19140).

QUESTION OR COMMENTS

1-800-289-8343